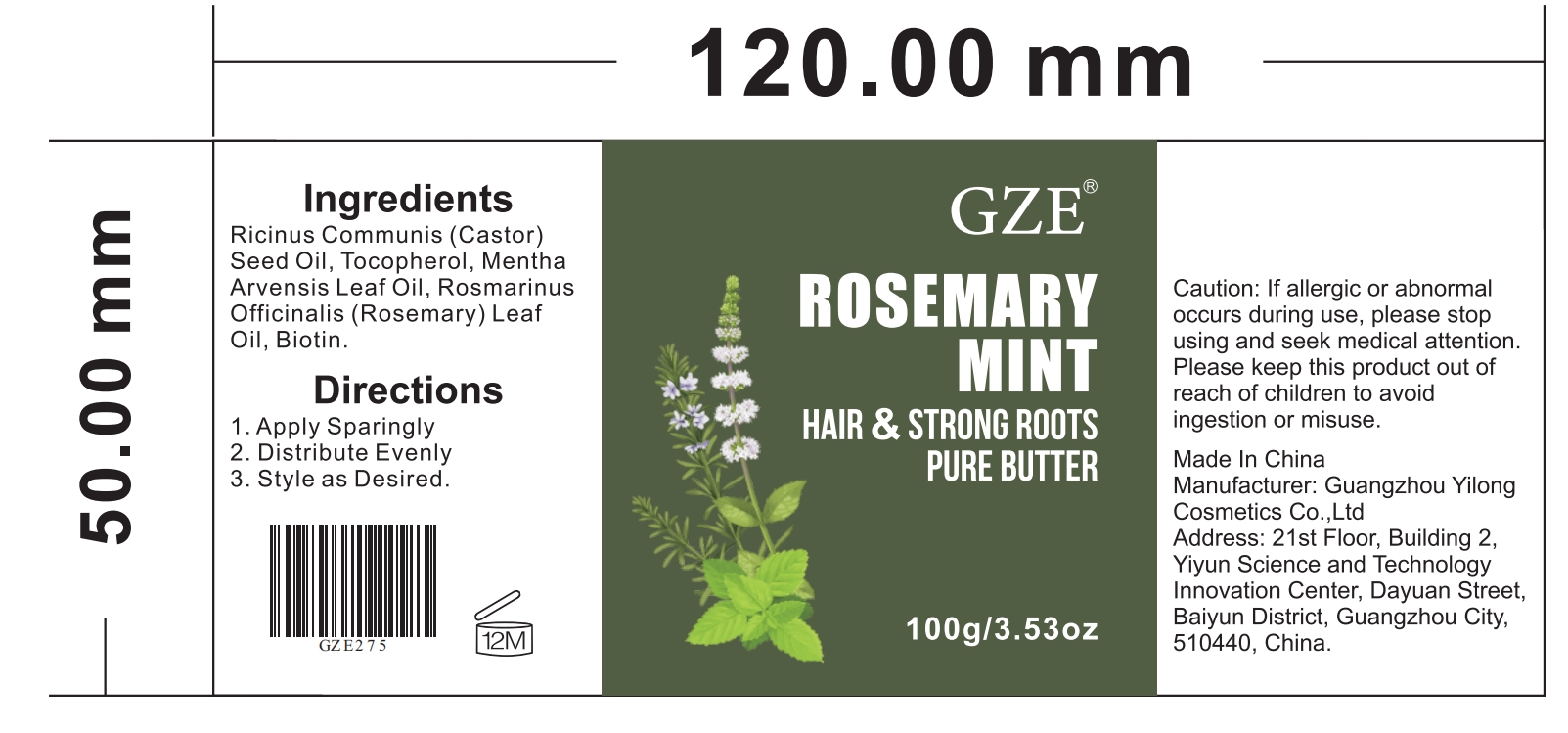 DRUG LABEL: GZE ROSEMARY MINT HAIR STRONG ROOTS PURE BUTTER
NDC: 74458-275 | Form: CREAM
Manufacturer: Guangzhou Yilong Cosmetics Co., Ltd
Category: otc | Type: HUMAN OTC DRUG LABEL
Date: 20241011

ACTIVE INGREDIENTS: BIOTIN 5 g/100 g; ROSEMARY OIL 10 g/100 g
INACTIVE INGREDIENTS: MENTHA ARVENSIS LEAF OIL; CASTOR OIL; TOCOPHEROL

GZE ROSEMARY MINT HAIR STRONG ROOTS PURE BUTTER

INDICATIONS AND USAGE

1. Apply Sparingly 2. Distribute Evenly 3. Style as Desired.

ACTIVE INGREDIENT

Rosemary Oil

Biotin.

INACTIVE INGREDIENT

Ricinus Communis (Castor) Seed Oil

Tocopherol

Mentha Arvensis Leaf Oil

PURPOSE

Strengthens hair and repairs dry hair problems.

WARNINGS

For external use only.

Stop use and ask a doctor if rash occurs.

Do not use on damaged or broken skin.

When using this product keep out of eyes. Rinse with water to remove.

Keep out of reach of children. If swallowed, get medical help or contact a Poison Control Center right away.

DOSAGE AND ADMINISTRATION

1. Apply Sparingly 2. Distribute Evenly 3. Style as Desired.